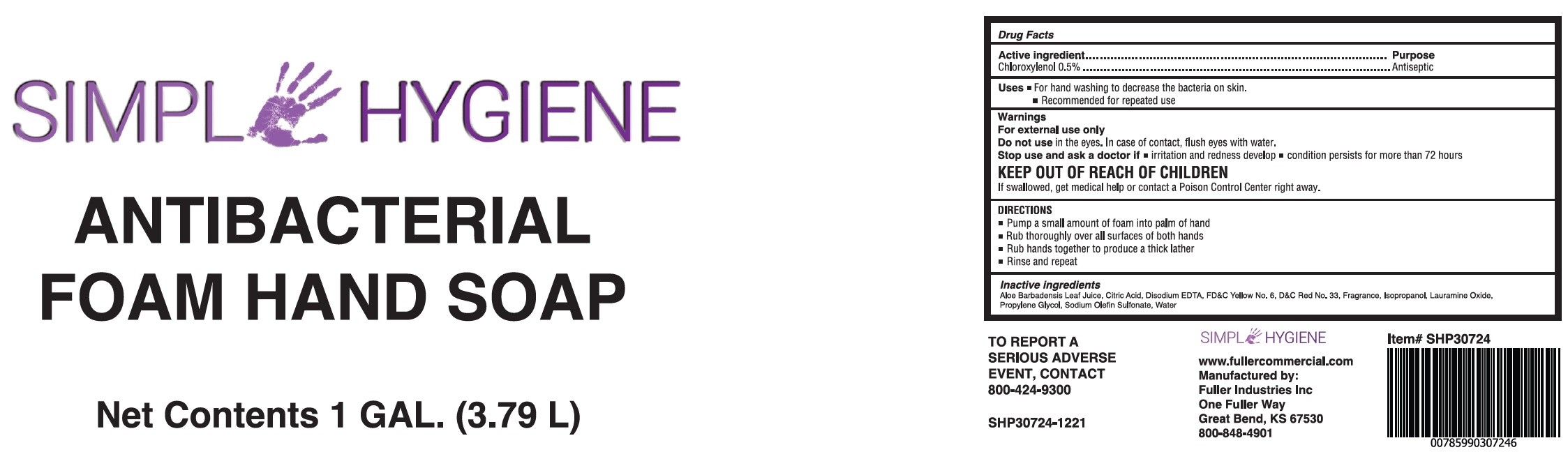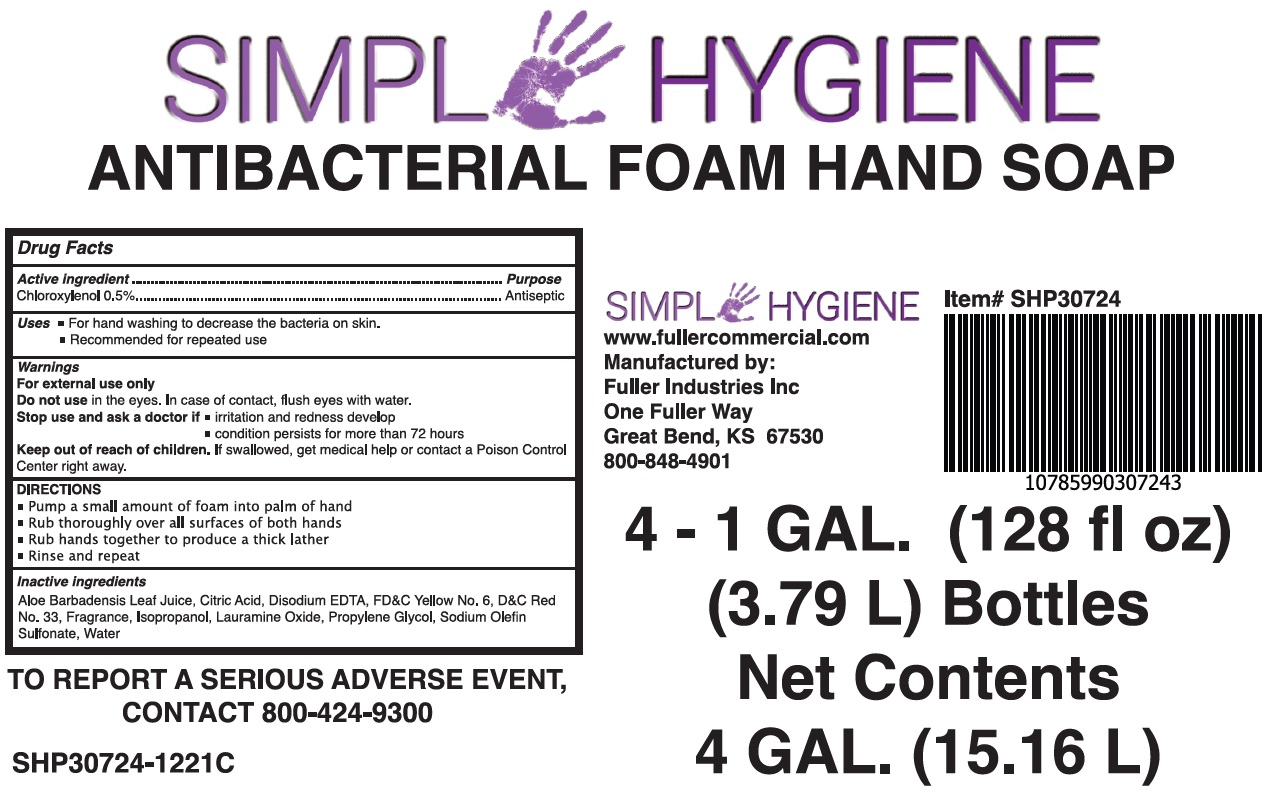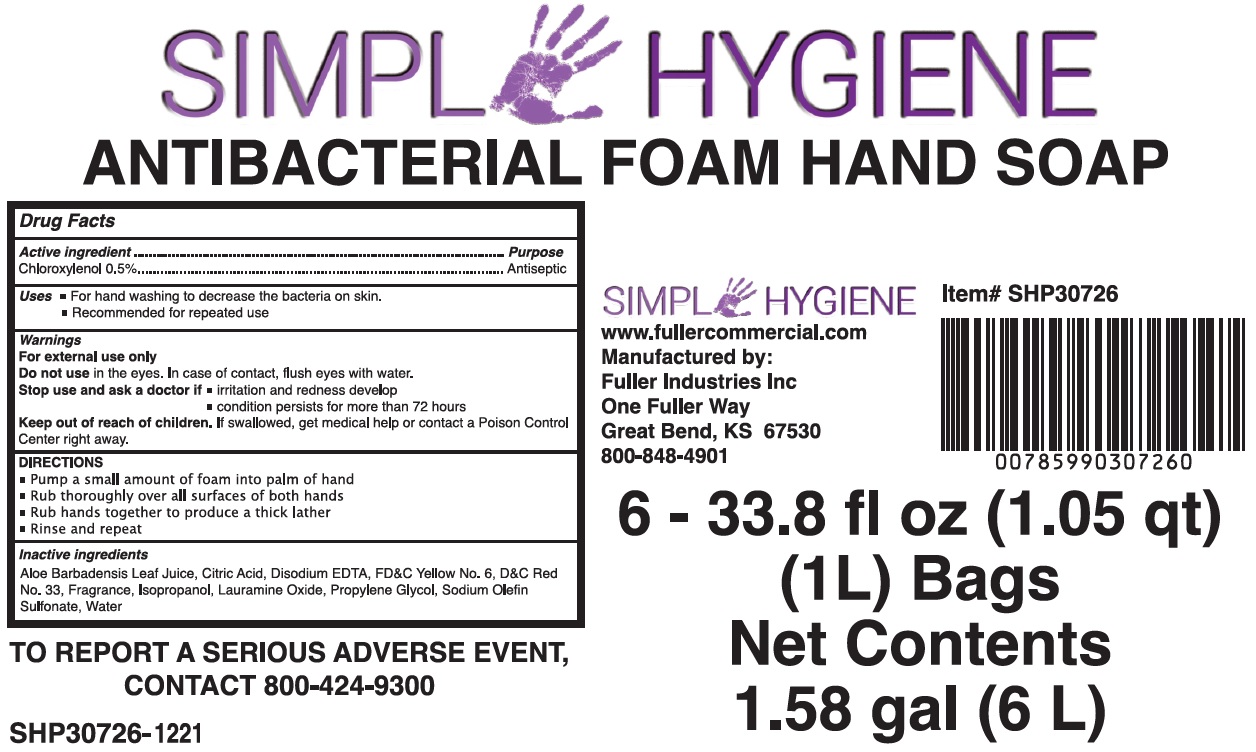 DRUG LABEL: Simple Hygiene Antibacterial Foam Hand
NDC: 60933-106 | Form: SOAP
Manufacturer: Fuller Industries, LLC
Category: otc | Type: HUMAN OTC DRUG LABEL
Date: 20231028

ACTIVE INGREDIENTS: CHLOROXYLENOL 5 mg/1 mL
INACTIVE INGREDIENTS: ALOE VERA LEAF; CITRIC ACID MONOHYDRATE; EDETATE DISODIUM ANHYDROUS; FD&C YELLOW NO. 6; D&C RED NO. 33; ISOPROPYL ALCOHOL; LAURAMINE OXIDE; PROPYLENE GLYCOL; WATER

Simple Hygiene Antibacterial Foam Hand Soap

Active ingredient

Chloroxylenol 0.5%

Purpose

Antiseptic

Uses

- For hand washing to decrease the bacteria on skin.
- Recommended for repeated use

Warnings

For external use only

Do not use

in the eyes. In case of contact, flush eyes with water.

Stop use and ask a doctor if

- irritatation and redness develop
- condition persists for more than 72 hours

Keep out of reach of children.

If swallowed, get medical help or contact a Poison Control Center right away.

DIRECTIONS

- Pump a small amount of foam into palm of hand
- Rub thoroughly over all surfaces of both hands
- Rub hands together to produce a thick lather
- Rinse and repeat

Inactive Ingerdients

Aloe Barbadensis Leaf Juice, Citric Acid, Disodium EDTA, FD&C Yellow No. 6, D&C Red No. 33, Fragrance, Isopropanol, Lauramine Oxide, Propylene Glycol, Sodium Oletin Sulfonate, Water